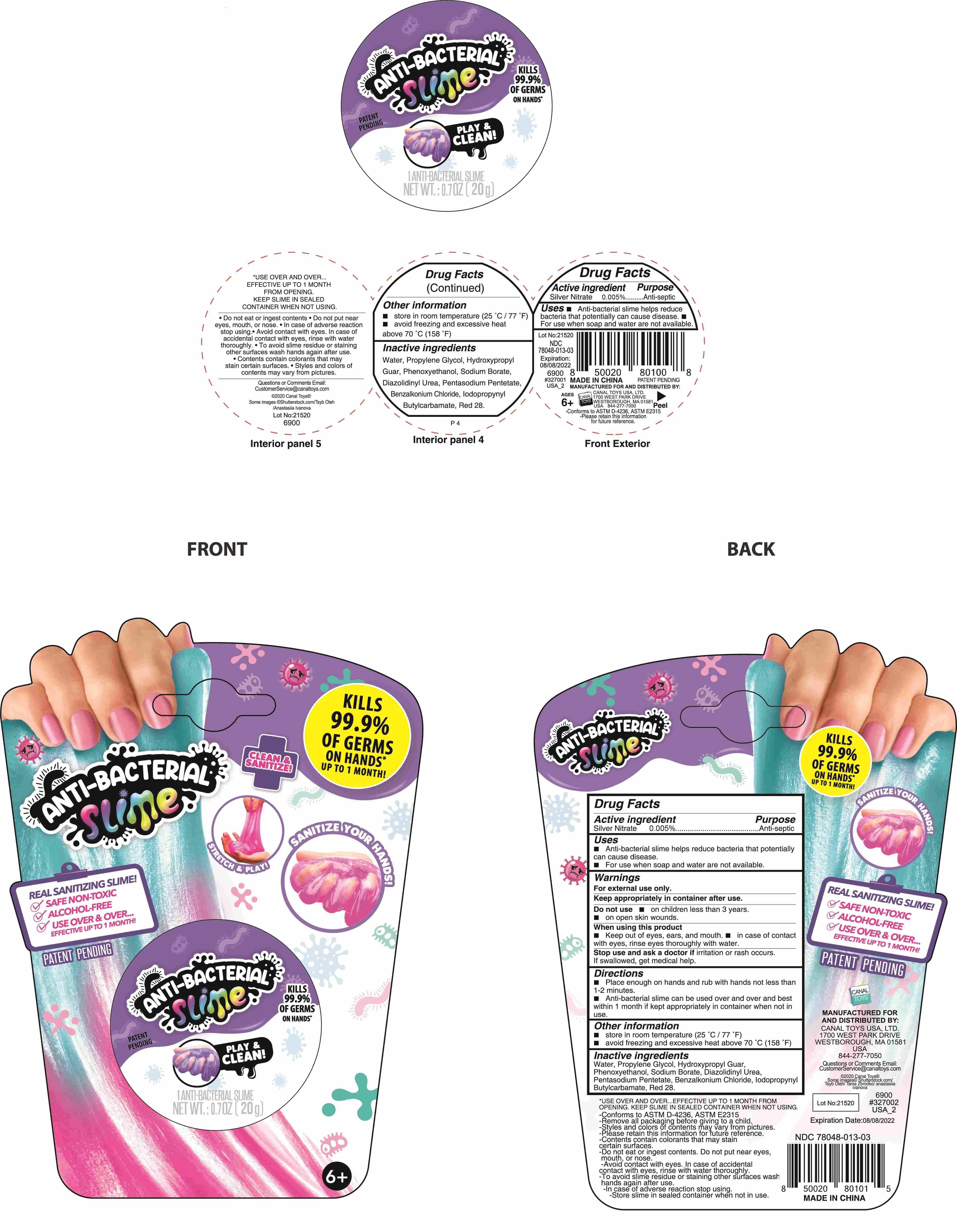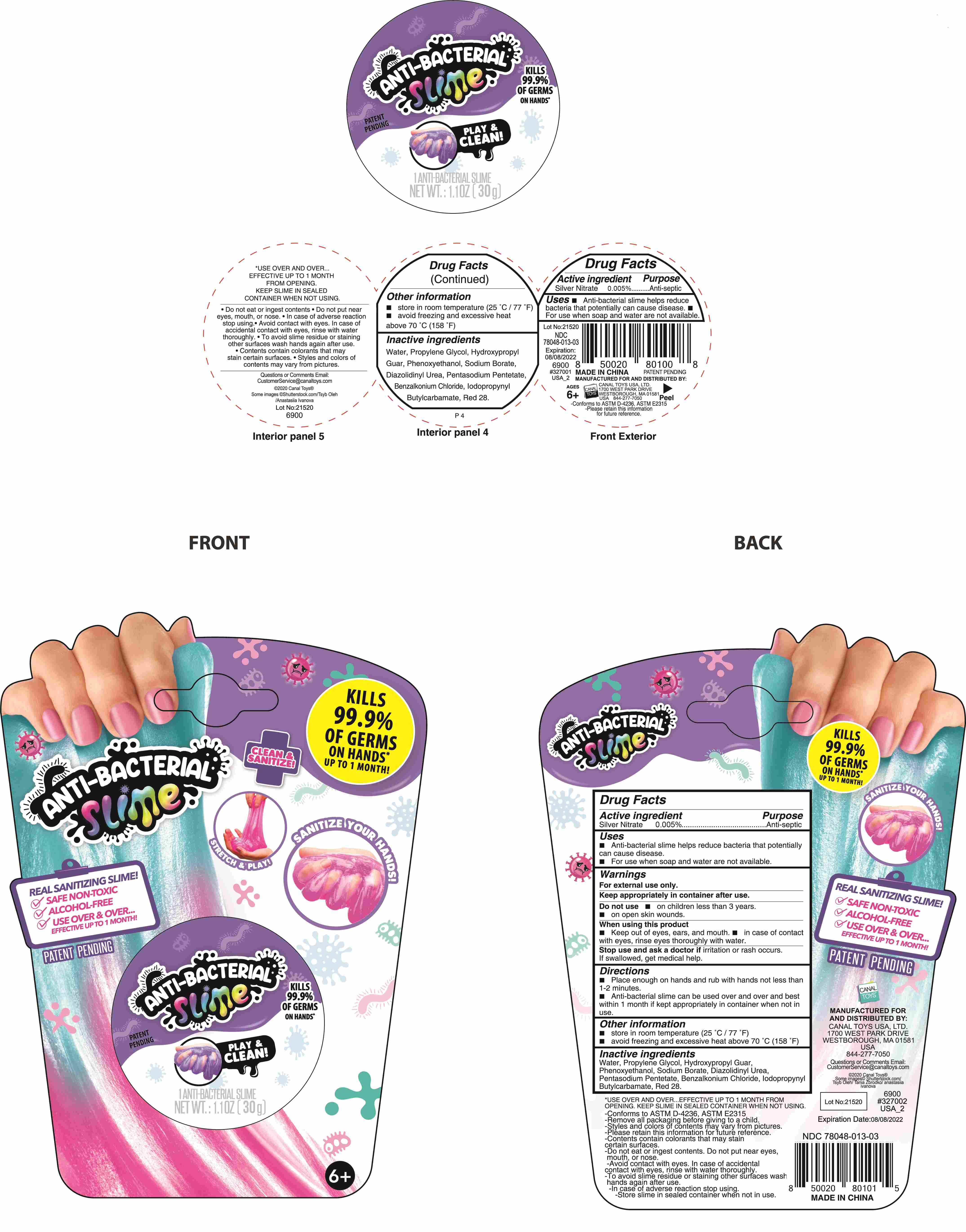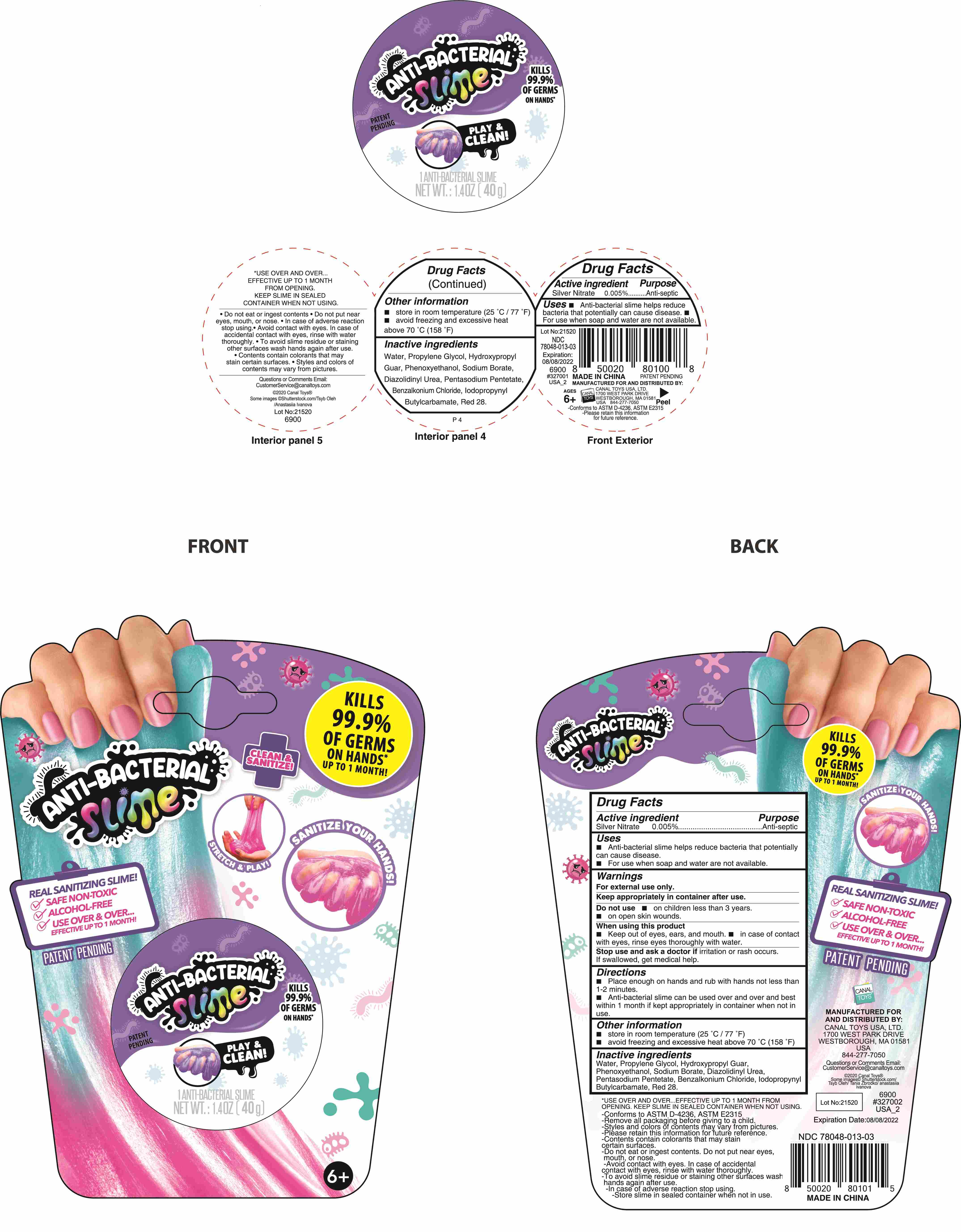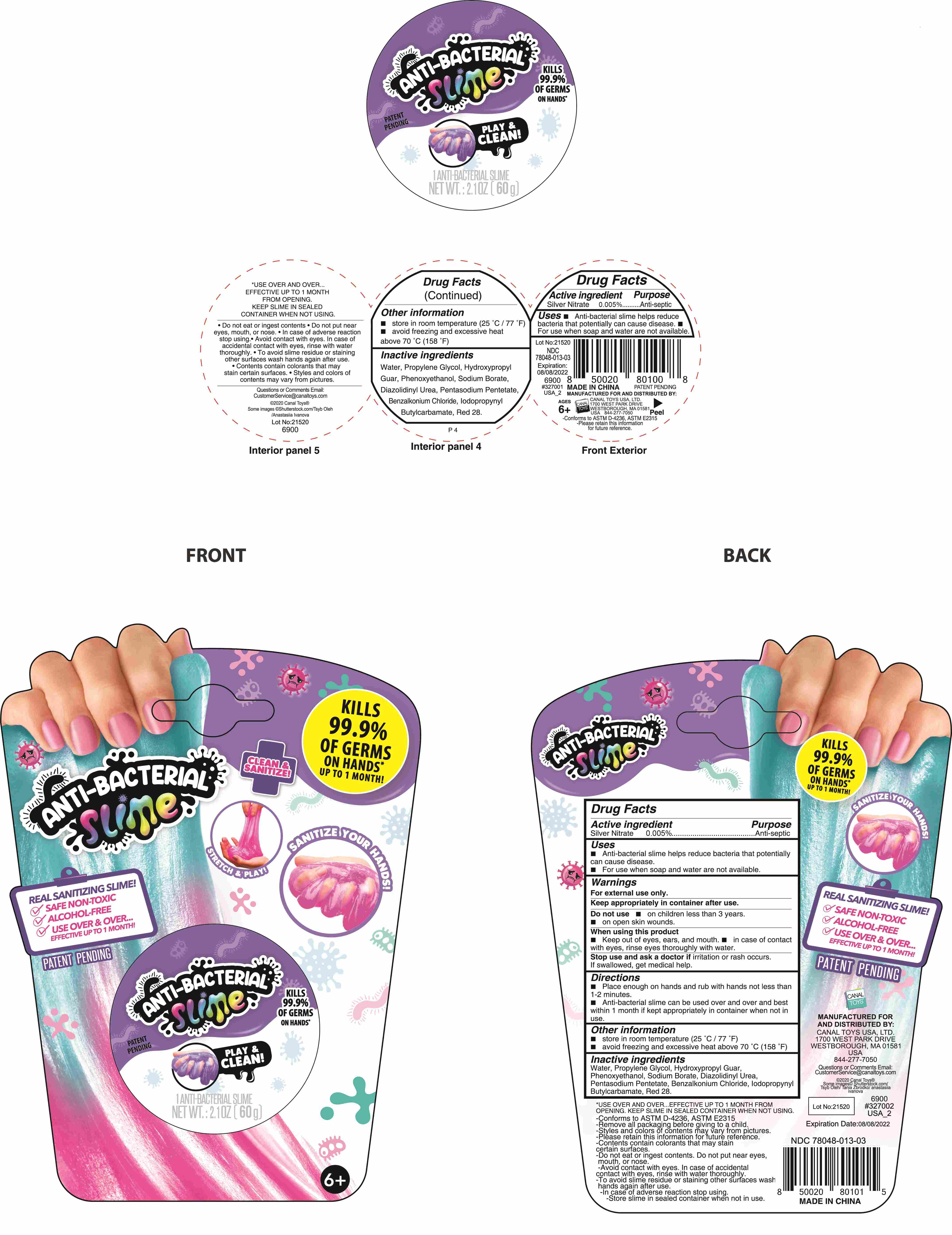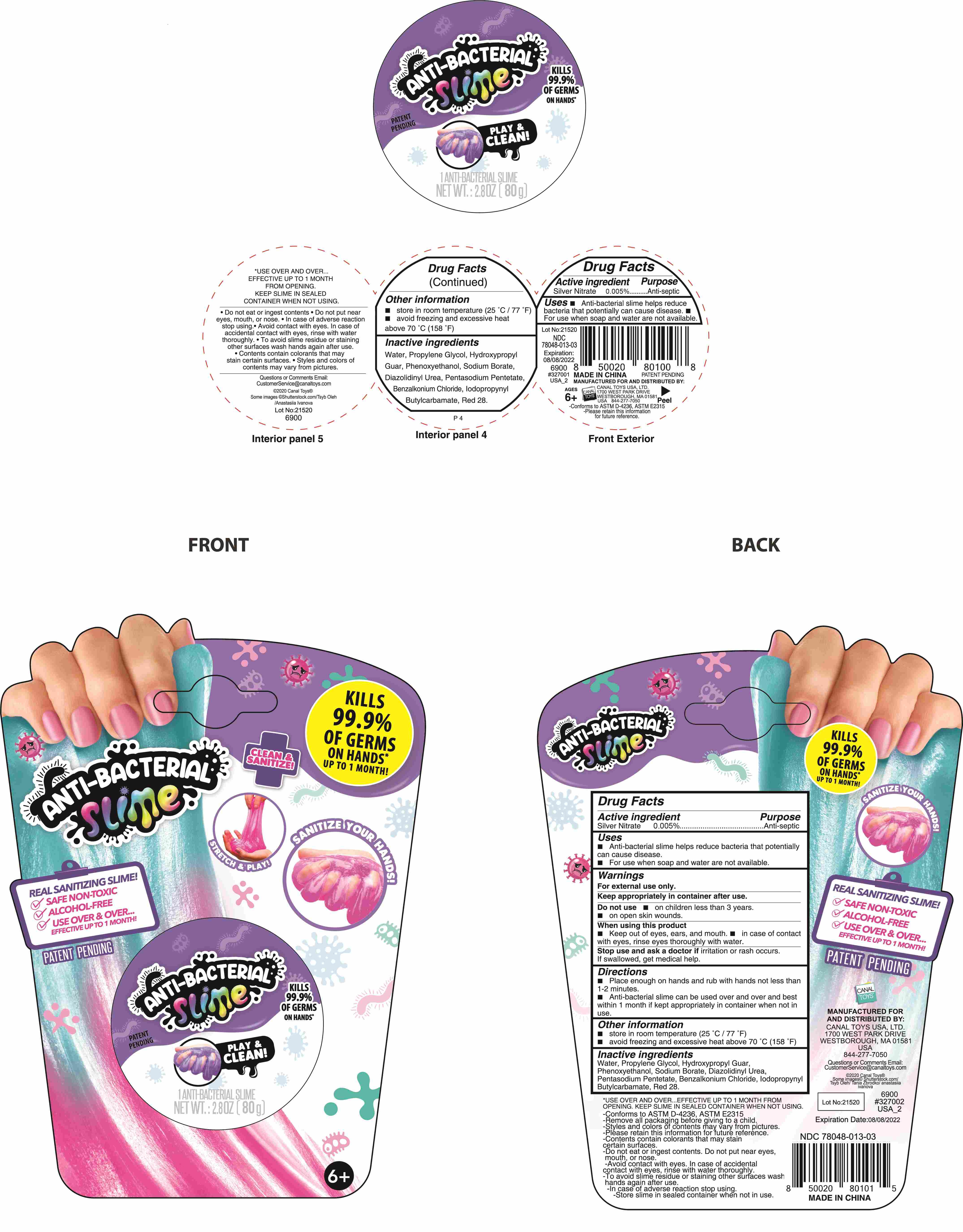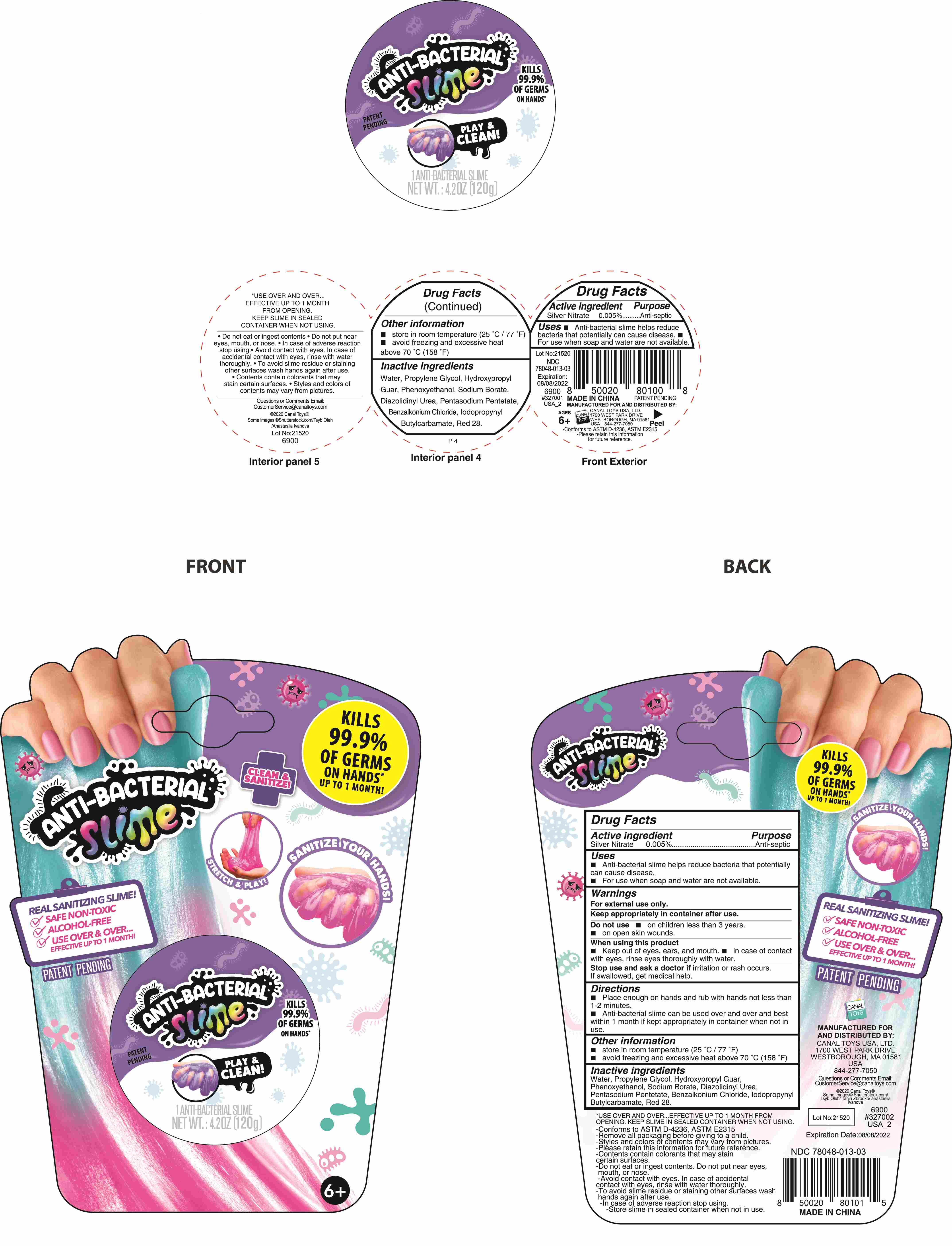 DRUG LABEL: ANTI-BACTERIAL SLIME
NDC: 78048-014 | Form: GEL
Manufacturer: Dongguan City Dexu Toys Co., Ltd.
Category: otc | Type: HUMAN OTC DRUG LABEL
Date: 20200906

ACTIVE INGREDIENTS: SILVER NITRATE 0.005 g/100 g
INACTIVE INGREDIENTS: PENTASODIUM PENTETATE; DIAZOLIDINYL UREA; GUARAPROLOSE (1300 MPA.S AT 1%); WATER; SODIUM BORATE; PROPYLENE GLYCOL; BENZALKONIUM CHLORIDE; PHENOXYETHANOL; IODOPROPYNYL BUTYLCARBAMATE; D&C RED NO. 28

78048-014
ANTI-BACTERIAL SLIME

Active Ingredient(s)

Silver Nitrate 0.005%

Purpose

Anti-septic

Use

Anti-bacterial slime helps reduce bateria that potentially can cause disease.
For use when soap and water are not available.

Warnings

For external use only.
Keep appropriately in container after use.

Do not use

in children less than 3.
on open skin wounds.

WHEN USING

Keep out of eyes, ears, and mouth.
in case of contact with eyes, rinse eyes thoroughly with water.

Stop use and ask a doctor if irritation or rash occurs.
If swallowed, get medical help.

Directions

place enough on hands and rub hands together not less than 1- 2 minutes.hands dry.
Supervise children under 3 years of age when using this product to avoid swallowing.
anti-bacterial slime can be used over and over and best within 1 months if keep appropriately in container whenever after use.

Other information

store in room temperature (25 C/77 F)
avoid freezing and excessive heat above 70 C (158 F)

Inactive ingredients

water, Propylene glycol, Hydroxypropyl Guar, Phenoxyethanol, Sodium Borate, Diazolidinyl Urea,
pentasodium pentetate, benzalkonium chloride, iodopropynyl Butylcarbamate, red 28